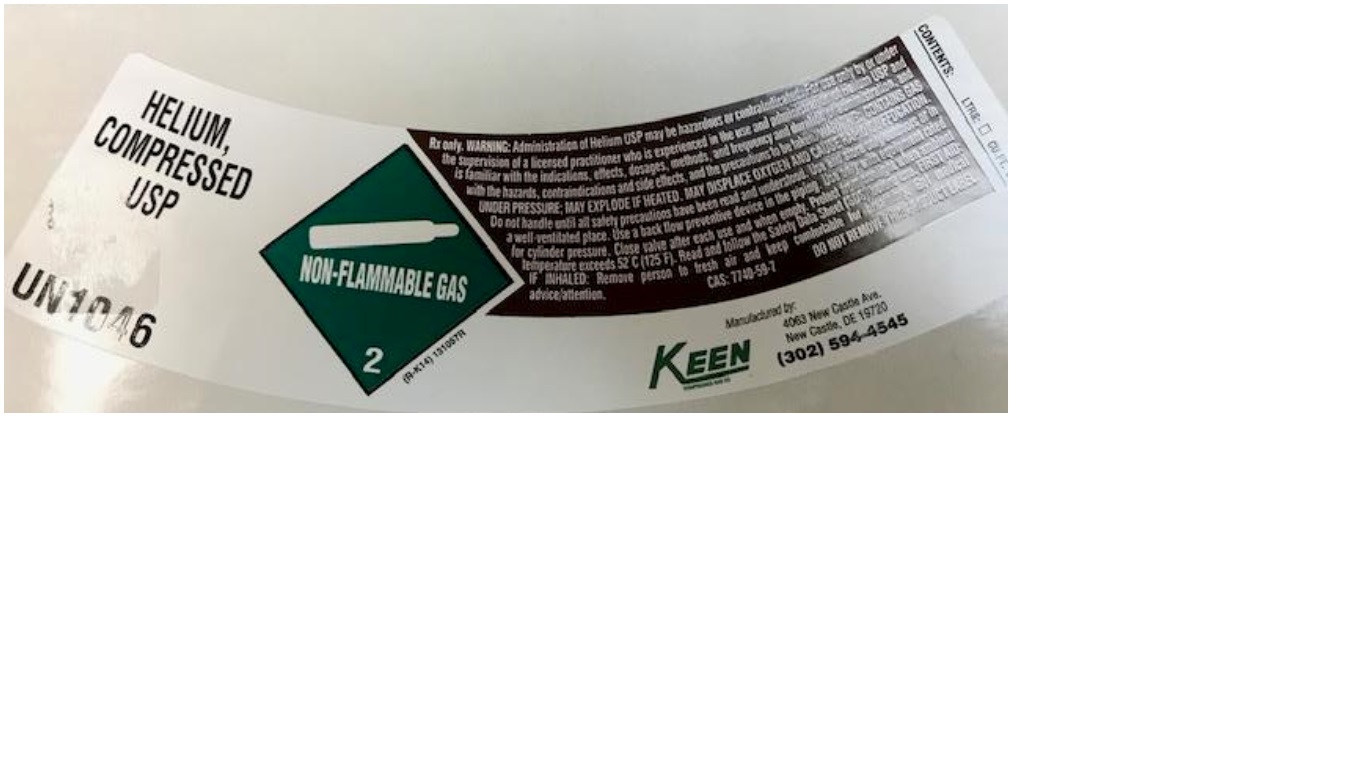 DRUG LABEL: Helium
NDC: 48273-011 | Form: GAS
Manufacturer: Keen Compressed Gas Co. Inc.
Category: prescription | Type: HUMAN PRESCRIPTION DRUG LABEL
Date: 20251117

ACTIVE INGREDIENTS: HELIUM 990 mL/1 L

Helium

PACKAGE LABEL

HELIUM, COMPRESSED USP

UN1046

Rx only. WARNING: Administration of Helium USP may be hazardous or contraindicated. For use only by or under the supervision of a licensed practitioner who is experienced in the use and administration of Helium USP and is familiar with the indications, effects, dosages, methods, and frequency and duration of administration, and with the hazards, contraindications and side effects, and the precautions to be taken. WARNING: CONTAINS GAS UNDER PRESSURE; MAY EXPLODE IF HEATED. MAY DISPLACE OXYGEN AND CAUSE RAPID SUFFOCATION. Do not handle until all safety precautions have been read and understood. Use and store only outdoors or in a well-ventilated place. Use a back flow preventive device in the piping. Use only with equipment rated for cylinder pressure. Close valve after each use and when empty. Protect from sunlight when ambient temperature exceeds 52 C (125 F). Read and follow the Safety Data Sheet (SDS) before use. FIRST AID: IF INHALED: Remove person to fresh air and keep comfortable for breathing. Get medical advice/attention.

CAS: 7740-59-7 DO NOT REMOVE THIS PRODUCT LABEL.

Manufactured by:

KEEN COMPRESSED GAS CO

4063 New Castle Ave. New Castle, DE 19720

(302) 594-4545